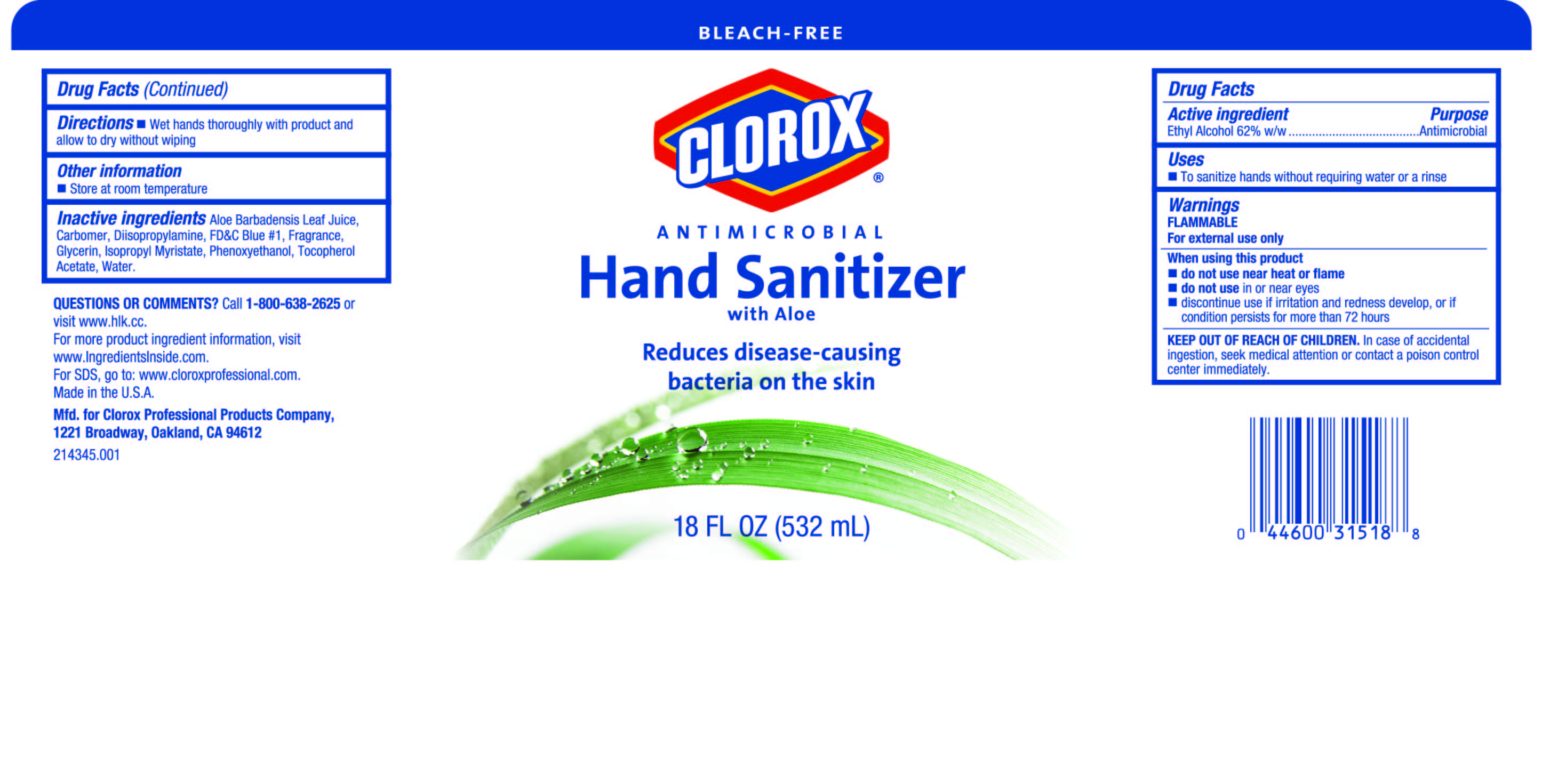 DRUG LABEL: Clorox Antimicrobial Hand Sanitizer
NDC: 26509-0010 | Form: GEL
Manufacturer: The Clorox Company
Category: otc | Type: HUMAN OTC DRUG LABEL
Date: 20160125

ACTIVE INGREDIENTS: ALCOHOL 620 mg/1 mL
INACTIVE INGREDIENTS: ALOE VERA LEAF; ISOPROPYL MYRISTATE; ALPHA-TOCOPHEROL ACETATE; WATER; DIISOPROPANOLAMINE; FD&C BLUE NO. 1; GLYCERIN; PHENOXYETHANOL; CARBOMER INTERPOLYMER TYPE A (55000 CPS)

Drug Facts

ACTIVE INGREDIENT

Ethyl Alcohol 62% w/w

PURPOSE

Antimicrobial

Uses

• To sanitize hands without requiring water or a rinse

Warnings

FLAMMABLE

For external use only

When using this product

• do not use near heat or flame

• do not use in or near eyes

• discontinue use if irritation and redness develop, or if condition persists for more than 72 hours

KEEP OUT OF REACH OF CHILDREN. In case of accidental ingestion, seek medical attention or contact a poison control center immediately.

Directions

• Wet hands thoroughly with product and allow to dry without wiping

Other Information

• Store at room temperature

Inactive ingredients

- Aloe Barbadensis Leaf Juice
- Carbomer
- Diisopropylamine
- FD&C Blue #1
- Fragrance
- Glycerin
- Isopropyl Myristate
- Phenoxyethanol
- Tocopherol Acetate
- Water

QUESTIONS OR COMMENTS?

Call 1-800-638-2625 or visit www.hlk.cc

PACKAGE LABEL

Clorox Antimicrobial Hand Sanitizer

18 FL OZ (532 mL)